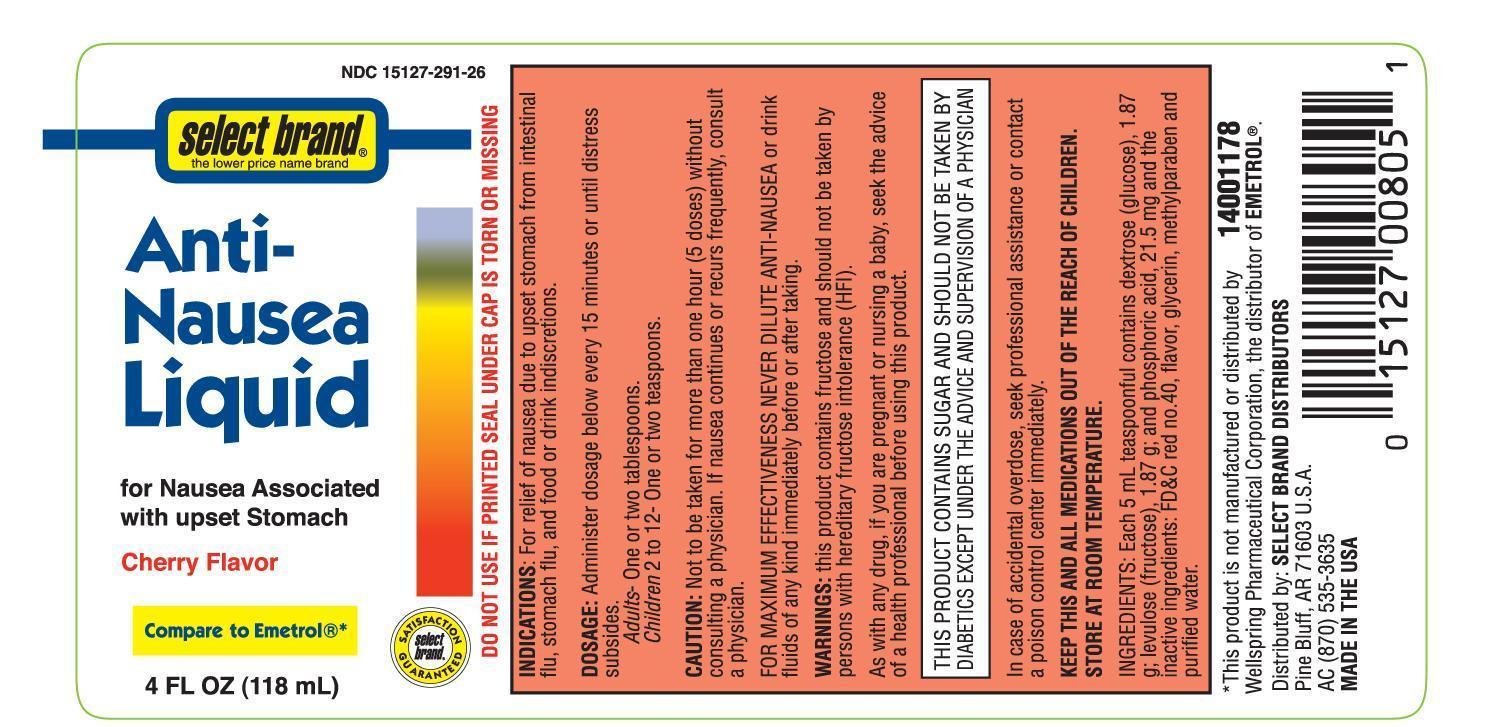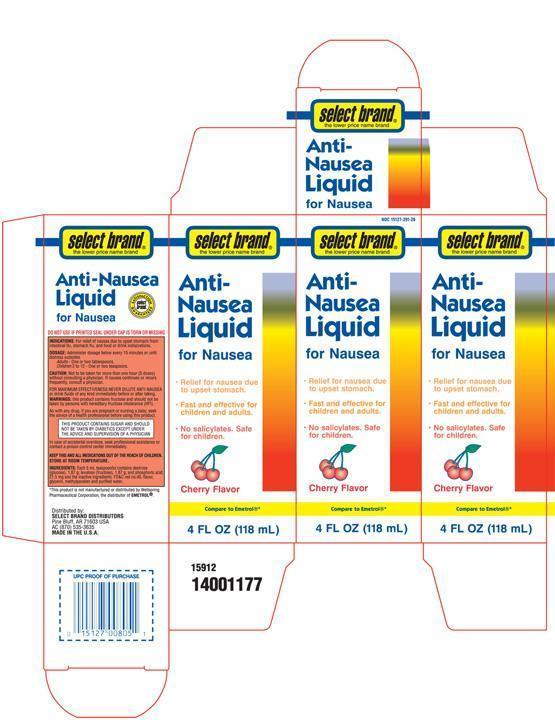 DRUG LABEL: Select Brand Anti-Nausea
NDC: 15127-291 | Form: SOLUTION
Manufacturer: L&R Distributors
Category: otc | Type: HUMAN OTC DRUG LABEL
Date: 20201222

ACTIVE INGREDIENTS: SUCROSE 3.74 g/5 mL; PHOSPHORIC ACID 21.5 mg/5 mL
INACTIVE INGREDIENTS: WATER; GLYCERIN; METHYLPARABEN; FD&C RED NO. 40

Select Brand Anti-Nausea Liquid

Active ingredients

Phosphorated carbohydrate solution*
*Each 5 mL contains:
• 3.74g Total sugar
• 21.5mg Phosphoric acid

Purpose

Upset stomach reliever

Uses

For relief of nausea due to upset stomach from intestinal flu, stomach flu, and food or drink indiscretions.

Warnings

- this product contains fructose and should not be taken by persons with hereditary fructose intolerance (HFI).

Stop use and ask a doctor if

- symptoms persist, return or get worse

KEEP THIS AND ALL MEDICATIONS OUT OF THE REACH OF CHILDREN.

In case of accidental overdose, seek professional assistance or contact a Poison Control Center right away.

DOSAGE: Administer dosage below every 15 miutes or until distress subsides.

Adults - One or two tablespoons.

Children 2 to 12 - One or two teaspoons.

Other information

Store at room temperature

Inactive ingredients

FD&C Red No 40, flavor, glycerin, methylparaben, and purified water.

PACKAGE LABEL

Lable